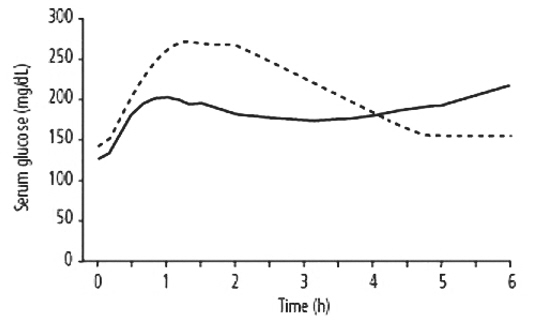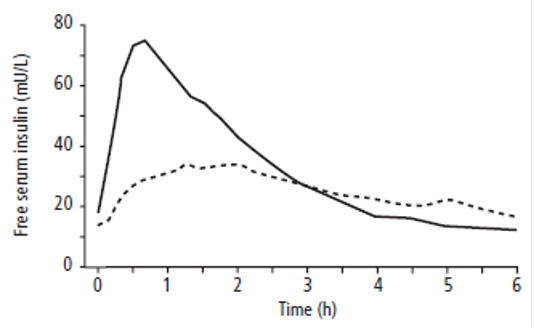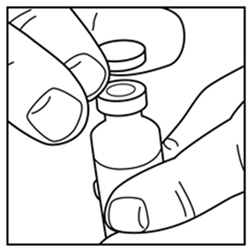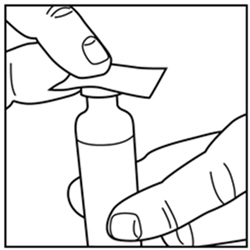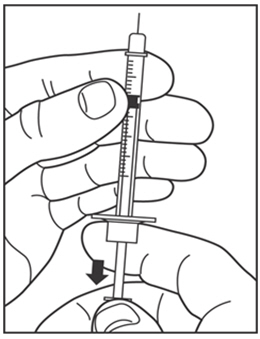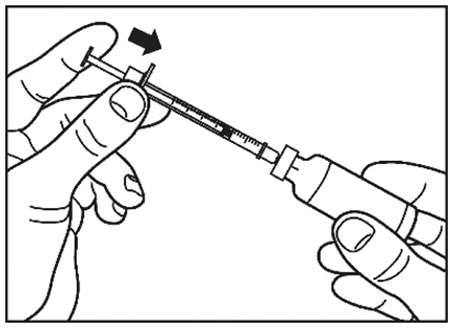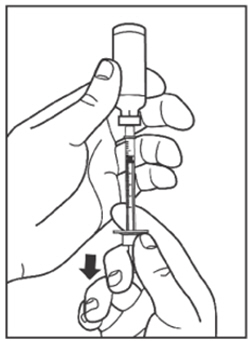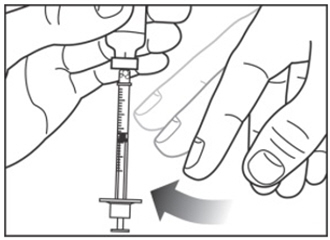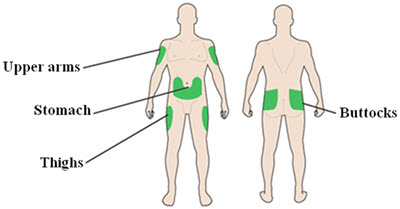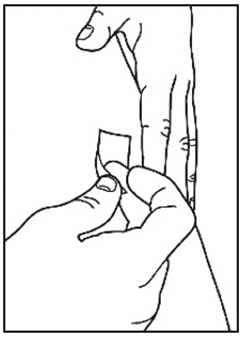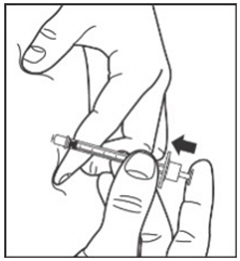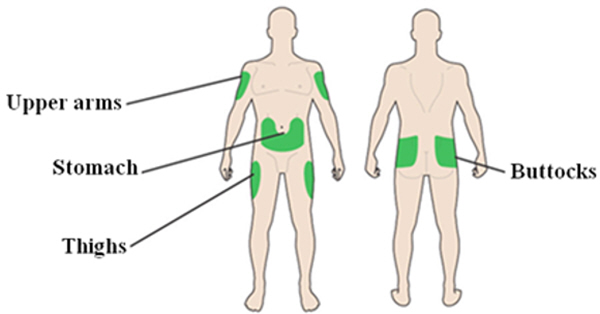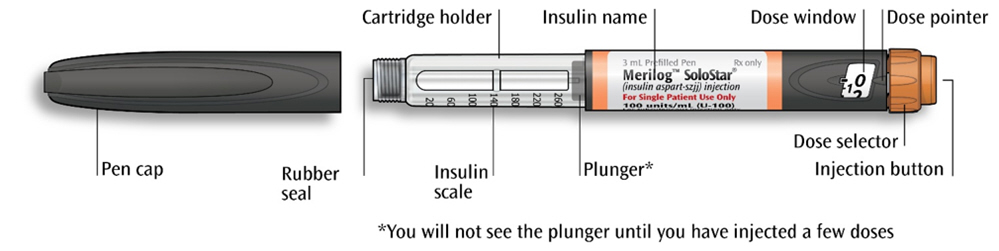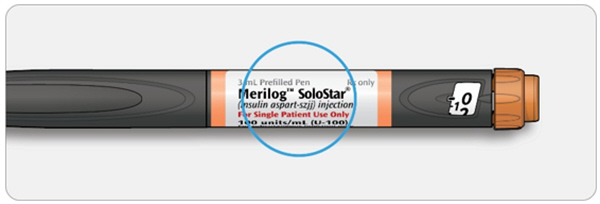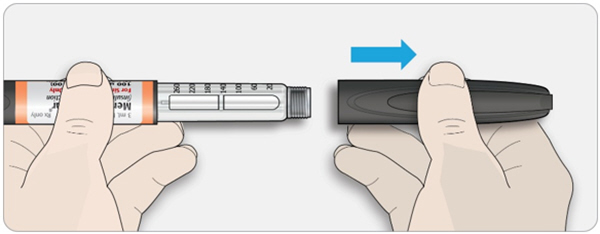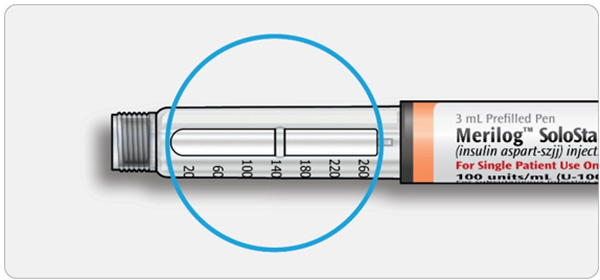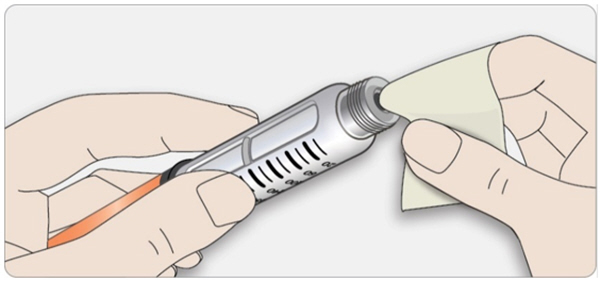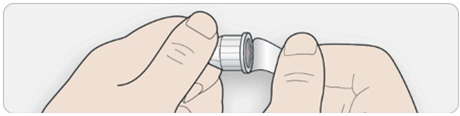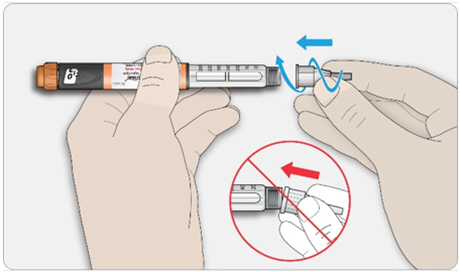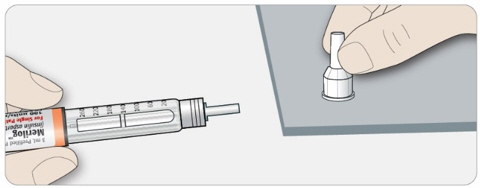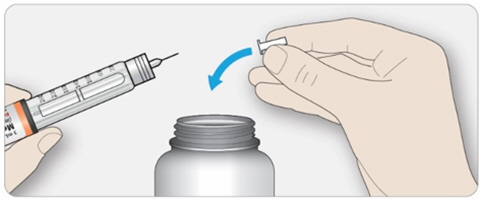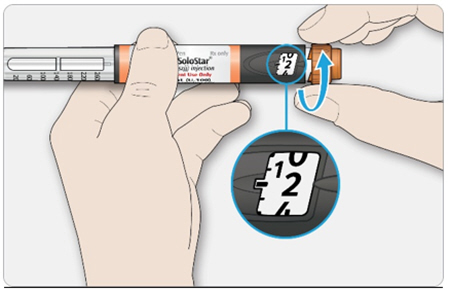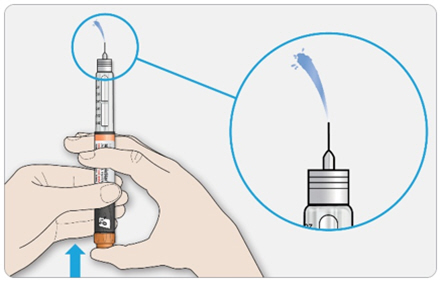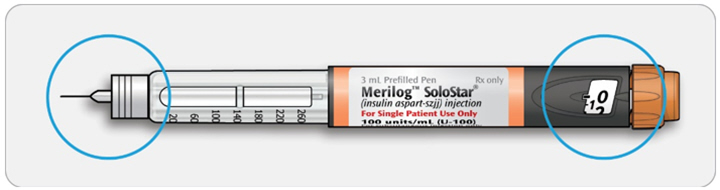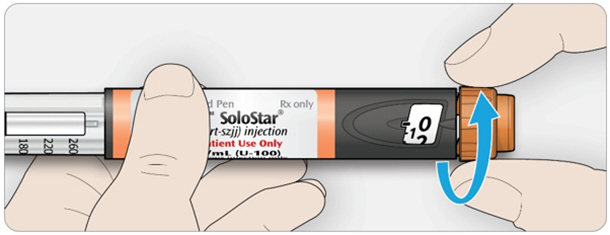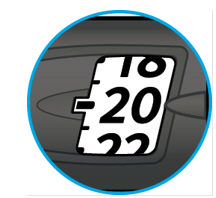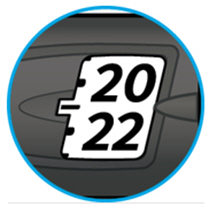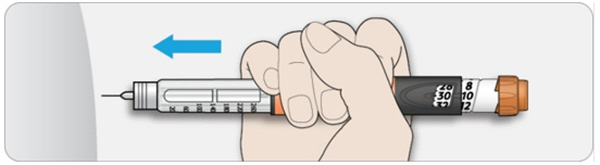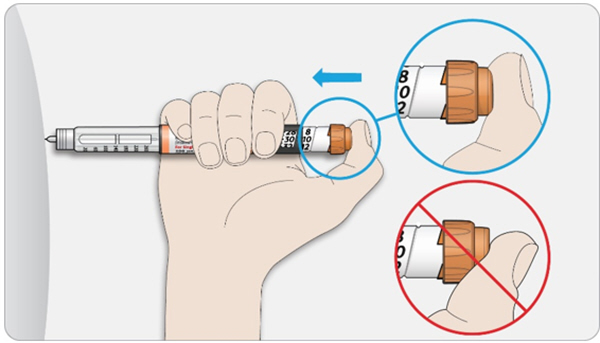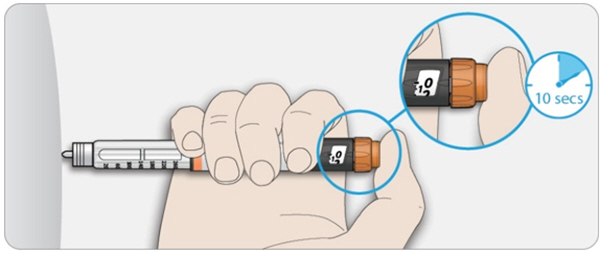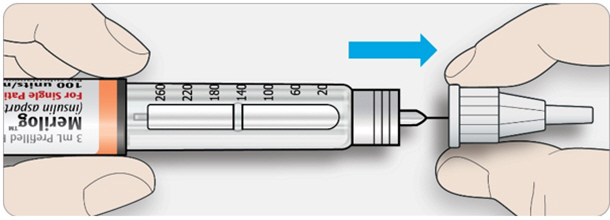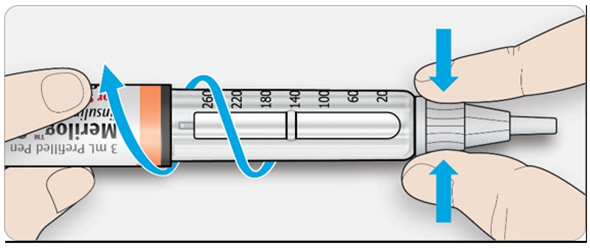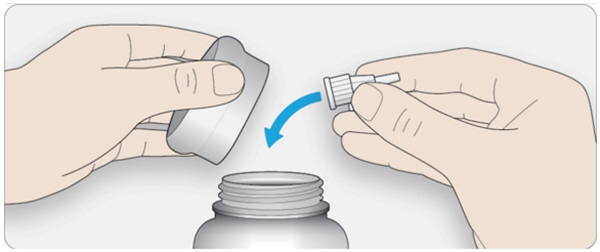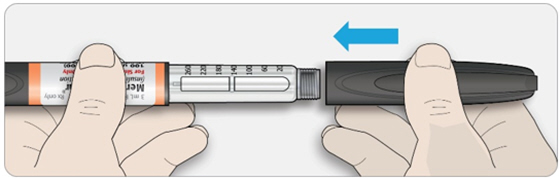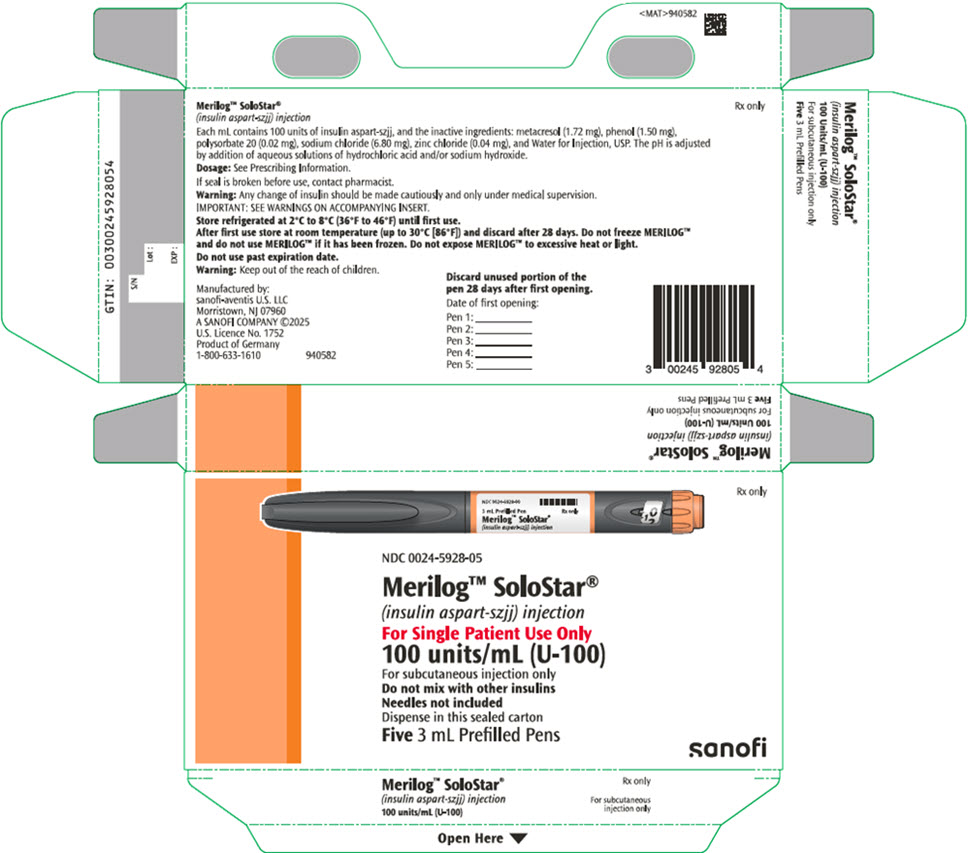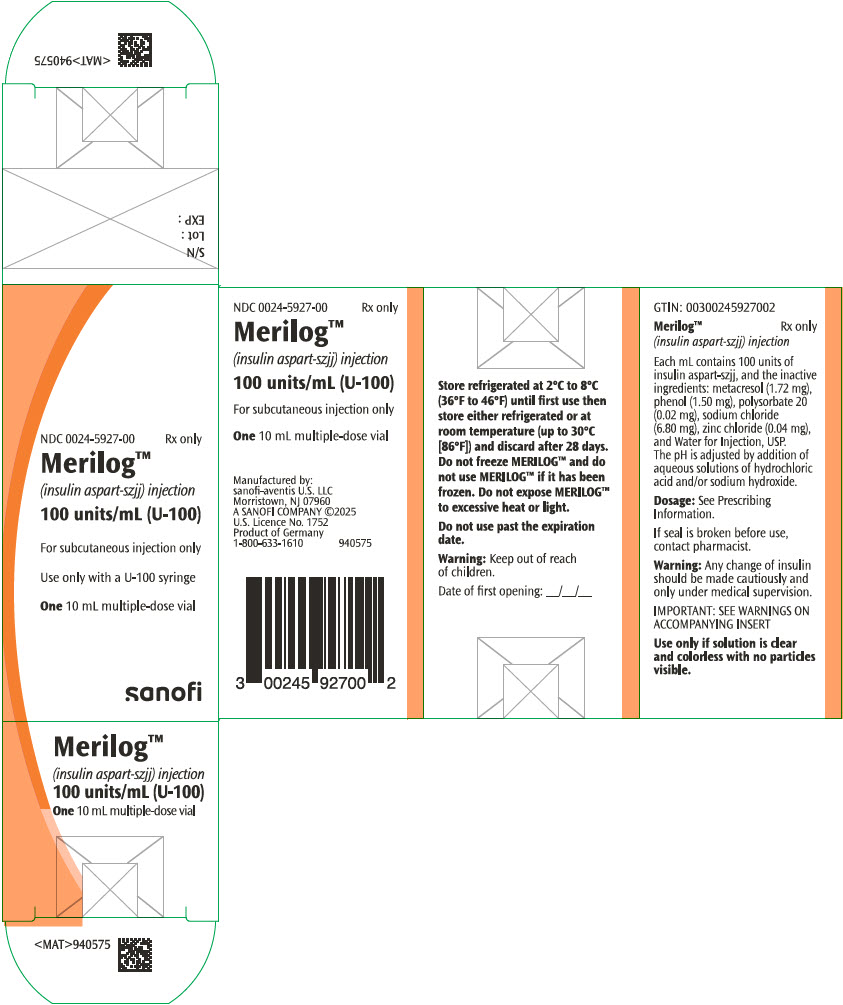 DRUG LABEL: MERILOG
NDC: 0024-5927 | Form: INJECTION, SOLUTION
Manufacturer: Sanofi-Aventis U.S. LLC
Category: prescription | Type: HUMAN PRESCRIPTION DRUG LABEL
Date: 20251007

ACTIVE INGREDIENTS: INSULIN ASPART 100 [iU]/1 mL
INACTIVE INGREDIENTS: METACRESOL 1.72 mg/1 mL; PHENOL 1.5 mg/1 mL; POLYSORBATE 20 0.02 mg/1 mL; SODIUM CHLORIDE 6.8 mg/1 mL; ZINC CHLORIDE 0.04 mg/1 mL; WATER

HIGHLIGHTS OF PRESCRIBING INFORMATION

These highlights do not include all the information needed to use MERILOG safely and effectively. See full prescribing information for MERILOG™.
MERILOG (insulin aspart-szjj) injection, for subcutaneous use.
Initial U.S. Approval: 2025
MERILOG™ (insulin aspart-szjj) is biosimilar [Biosimilar means that the biological product is approved based on data demonstrating that it is highly similar to an FDA-approved biological product, known as a reference product, and that there are no clinically meaningful differences between the biosimilar product and the reference product. Biosimilarity of MERILOG has been demonstrated for the condition(s) of use (e.g., indication (s), dosing regimen(s)), strength(s), dosage form(s), and route(s) of administration described in its Full Prescribing Information.] to NOVOLOG® (insulin aspart).

1 INDICATIONS AND USAGE

MERILOG is rapid acting human insulin analog indicated to improve glycemic control in adults and pediatric patients with diabetes mellitus (1).

2 DOSAGE AND ADMINISTRATION

See Full Prescribing Information for important preparation, administration, and dosage instructions (2.1, 2.2, 2.3, 2.4, 2.5).

- Subcutaneous injection (2.2):
  - Inject subcutaneously within 5–10 minutes before a meal into the abdominal area, thigh, buttocks or upper arm.
  - Rotate injection sites within the same region from one injection to the next to reduce risk of lipodystrophy and localized cutaneous amyloidosis.
  - Should generally be used in regimens with an intermediate- or long-acting insulin.
- Individualize and adjust the dosage of MERILOG based on the individual's metabolic needs, blood glucose monitoring results and glycemic control goal (2.3).
- Dosage adjustments may be needed with changes in physical activity, changes in meal patterns (i.e., macronutrient content or timing of food intake), changes in renal or hepatic function or during acute illness (2.3).

3 DOSAGE FORMS AND STRENGTHS

Injection: 100 units/mL (U-100) of insulin aspart-szjj available as: (3)

- 10 mL multiple-dose vial
- 3 mL single-patient-use MERILOG SoloStar® prefilled pen

4 CONTRAINDICATIONS

- During episodes of hypoglycemia (4).
- Hypersensitivity to insulin aspart products or any of the excipients in MERILOG.(4).

5 WARNINGS AND PRECAUTIONS

- Never share a MERILOG SoloStar prefilled pen between patients, even if the needle is changed (5.1).
- Hyperglycemia or hypoglycemia with changes in insulin regimen: Make changes to a patient's insulin regimen (e.g., insulin strength, manufacturer, type, injection site or method of administration) under close medical supervision with increased frequency of blood glucose monitoring (5.2).
- Hypoglycemia: May be life-threatening. Increase frequency of glucose monitoring with changes to: insulin dosage, concomitantly administered glucose lowering medications, meal pattern, physical activity; and in patients with renal or hepatic impairments and hypoglycemia unawareness (5.3).
- Medication Errors: Accidental mix-ups between insulin products can occur. Instruct patients to check insulin labels before injection (5.4).
- Hypersensitivity reactions: Severe, life-threatening, generalized allergy, including anaphylaxis, may occur. Discontinue MERILOG, treat, and monitor, if indicated (5.5).
- Hypokalemia: May be life-threatening. Monitor potassium levels in patients at risk of hypokalemia and treat if indicated (5.6).
- Fluid retention and heart failure with concomitant use of thiazolidinediones (TZDs): Observe for signs and symptoms of heart failure; consider dosage reduction or discontinuation if heart failure occurs (5.7).

6 ADVERSE REACTIONS

Adverse reactions observed with insulin aspart products include: hypoglycemia, allergic reactions, local injection site reactions, lipodystrophy, rash, and pruritus (6).

To report SUSPECTED ADVERSE REACTIONS, contact sanofi-aventis at 1-800-633-1610 or FDA at 1-800-FDA-1088 or www.fda.gov/medwatch.

7 DRUG INTERACTIONS

- Drugs that may increase the risk of hypoglycemia: Antidiabetic agents, ACE inhibitors, angiotensin II receptor blocking agents, disopyramide, fibrates, fluoxetine, monoamine oxidase inhibitors, pentoxifylline, pramlintide, salicylates, somatostatin analog (e.g., octreotide), and sulfonamide antibiotics (7).
- Drugs that may decrease the blood glucose lowering effect: Atypical antipsychotics, corticosteroids, danazol, diuretics, estrogens, glucagon, isoniazid, niacin, oral contraceptives, phenothiazines, progestogens (e.g., in oral contraceptives), protease inhibitors, somatropin, sympathomimetic agents (e.g., albuterol, epinephrine, terbutaline), and thyroid hormones (7).
- Drugs that may increase or decrease the blood glucose lowering effect: Alcohol, beta-blockers, clonidine, lithium salts, and pentamidine (7).
- Drugs that may blunt the signs and symptoms of hypoglycemia: Beta-blockers, clonidine, guanethidine, and reserpine (7).

FULL PRESCRIBING INFORMATION

1 INDICATIONS AND USAGE

MERILOG is indicated to improve glycemic control in adults and pediatric patients with diabetes mellitus.

2 DOSAGE AND ADMINISTRATION

2.1 Important Preparation and Administration Instructions

- Always check insulin labels before administration [see Warnings and Precautions (5.4)].
- Inspect MERILOG visually before use. It should appear clear and colorless. Do not use MERILOG if particulate matter or coloration is seen.
- Use MERILOG SoloStar prefilled pen with caution in patients with visual impairment who may rely on audible clicks to dial their dose.

2.2 Preparation and Administration Instructions for the Approved Routes of Administration

Subcutaneous Injection

- Inject MERILOG subcutaneously within 5–10 minutes before a meal into the abdominal area, thigh, buttocks or upper arm.
- Rotate injection sites within the same region from one injection to the next to reduce the risk of lipodystrophy and localized cutaneous amyloidosis. Do not inject into areas of lipodystrophy or localized cutaneous amyloidosis [see Warnings and Precautions (5.2) and Adverse Reactions (6.1, 6.3)].
- The MERILOG SoloStar prefilled pen dials in 1-unit increments.
- Generally use MERILOG (administered by subcutaneous injection) in regimens with an intermediate- or long-acting insulin.

2.3 Dosage Recommendations

- Individualize the dosage of MERILOG based on the patient's metabolic needs, blood glucose monitoring results and glycemic control goal.
- Dosage adjustments may be needed with changes in physical activity, changes in meal patterns (i.e., macronutrient content or timing of food intake), changes in renal or hepatic function or during acute illness [see Warnings and Precautions (5.2, 5.3) and Use in Specific Populations (8.6, 8.7)].
- When switching from another insulin to MERILOG, a different dosage of MERILOG may be needed [see Warnings and Precautions (5.2)].
- During changes to a patient's insulin regimen, increase the frequency of blood glucose monitoring [see Warnings and Precautions (5.2)].

2.4 Dosage Modifications for Drug Interactions

- Dosage modification may be needed when MERILOG is used concomitantly with certain drugs [see Drug Interactions (7)].

2.5 Instructions for Mixing MERILOG with Other Insulins

Do not mix MERILOG with any other insulin.

3 DOSAGE FORMS AND STRENGTHS

Injection: 100 units/mL (U-100) is a clear and colorless solution available as:

- 10 mL multiple-dose vial
- 3 mL single-patient-use MERILOG SoloStar® prefilled pen

4 CONTRAINDICATIONS

MERILOG is contraindicated:

- During episodes of hypoglycemia [see Warnings and Precautions (5.3)].
- In patients with hypersensitivity to insulin aspart products or any of the excipients in MERILOG [see Warnings and Precautions (5.5)].

5 WARNINGS AND PRECAUTIONS

5.1 Never Share a MERILOG SoloStar Prefilled Pen Between Patients

MERILOG SoloStar prefilled pen should never be shared between patients, even if the needle is changed. Patients using MERILOG vials must never share needles or syringes with another person. Sharing poses a risk for transmission of blood-borne pathogens.

5.2 Hyperglycemia or Hypoglycemia with Changes in Insulin Regimen

Changes in an insulin regimen (e.g., insulin strength, manufacturer, type, injection site or method of administration) may affect glycemic control and predispose to hypoglycemia [see Warnings and Precautions (5.3)] or hyperglycemia. Repeated insulin injections into areas of lipodystrophy or localized cutaneous amyloidosis have been reported to result in hyperglycemia; and a sudden change in the injection site (to an unaffected area) has been reported to result in hypoglycemia [see Adverse Reactions (6.1, 6.3)].

Make any changes to a patient's insulin regimen under close medical supervision with increased frequency of blood glucose monitoring. Advise patients who have repeatedly injected into areas of lipodystrophy or localized cutaneous amyloidosis to change the injection site to unaffected areas and closely monitor for hypoglycemia. For patients with type 2 diabetes, dosage adjustments of concomitant anti-diabetic products may be needed.

5.3 Hypoglycemia

Hypoglycemia is the most common adverse reaction of all insulins, including insulin aspart products. Severe hypoglycemia can cause seizures, may lead to unconsciousness, may be life threatening or cause death. Hypoglycemia can impair concentration ability and reaction time; this may place an individual and others at risk in situations where these abilities are important (e.g., driving or operating other machinery).

Hypoglycemia can happen suddenly and symptoms may differ in each individual and change over time in the same individual. Symptomatic awareness of hypoglycemia may be less pronounced in patients with longstanding diabetes in patients with diabetic nerve disease, in patients using medications that block the sympathetic nervous system (e.g., beta-blockers) [see Drug Interactions (7)], or in patients who experience recurrent hypoglycemia.

Risk Factors for Hypoglycemia

The risk of hypoglycemia after an injection is related to the duration of action of the insulin and, in general, is highest when the glucose lowering effect of the insulin is maximal. As with all insulins, the glucose lowering effect time course of insulin aspart products may vary in different individuals or at different times in the same individual and depends on many conditions, including the area of injection as well as the injection site blood supply and temperature [see Clinical Pharmacology (12.2)]. Other factors which may increase the risk of hypoglycemia include changes in meal pattern (e.g., macronutrient content or timing of meals), changes in level of physical activity, or changes to concomitantly administered medication [see Drug Interactions (7)]. Patients with renal or hepatic impairment may be at higher risk of hypoglycemia [see Use in Specific Populations (8.6, 8.7)].

Risk Mitigation Strategies for Hypoglycemia

Patients and caregivers must be educated to recognize and manage hypoglycemia. Self-monitoring of blood glucose plays an essential role in the prevention and management of hypoglycemia; increased frequency of blood glucose monitoring is recommended. In patients at higher risk for hypoglycemia and patients who have reduced symptomatic awareness of hypoglycemia, increased frequency of blood glucose monitoring is recommended.

5.4 Hypoglycemia Due to Medication Errors

Accidental mix-ups between insulin products have been reported. To avoid medication errors between MERILOG and other insulins, instruct patients to always check the insulin label before each injection.

5.5 Hypersensitivity Reactions

Severe, life-threatening, generalized allergy, including anaphylaxis, can occur with insulins, including insulin aspart products. If hypersensitivity reactions occur, discontinue MERILOG; treat per standard of care and monitor until symptoms and signs resolve [see Adverse Reactions (6)]. MERILOG is contraindicated in patients who have had hypersensitivity reactions to insulin aspart products or any of the excipients in MERILOG [see Contraindications (4)].

5.6 Hypokalemia

All insulins, including insulin aspart products, can cause a shift in potassium from the extracellular to intracellular space, possibly leading to hypokalemia. Untreated hypokalemia may cause respiratory paralysis, ventricular arrhythmia, and death. Monitor potassium levels in patients at risk for hypokalemia if indicated (e.g., patients using potassium-lowering medications, patients taking medications sensitive to serum potassium concentration).

5.7 Fluid Retention and Heart Failure with Concomitant Use of PPAR-gamma Agonists

Thiazolidinediones (TZDs), which are peroxisome proliferator-activated receptor (PPAR)-gamma agonists, can cause dose-related fluid retention, particularly when used in combination with insulin. Fluid retention may lead to or exacerbate heart failure. Patients treated with insulin, including MERILOG, and a PPAR-gamma agonist should be observed for signs and symptoms of heart failure. If heart failure develops, it should be managed according to current standards of care, and discontinuation or dose reduction of the PPAR-gamma agonist must be considered.

6 ADVERSE REACTIONS

The following adverse reactions are also discussed elsewhere:

- Hypoglycemia [see Warnings and Precautions (5.3)]
- Hypoglycemia Due to Medication Errors [see Warnings and Precautions (5.4)]
- Hypersensitivity Reactions [see Warnings and Precautions (5.5)]
- Hypokalemia [see Warnings and Precautions (5.6)]

6.1 Clinical Trials Experience

Because clinical trials are conducted under widely varying designs, the adverse reaction rates reported in one clinical trial may not be easily compared to those rates reported in another clinical trial, and may not reflect the rates actually observed in clinical practice. The safety of insulin aspart was evaluated in two treat-to-target trials of 6 months duration, conducted in patients with type 1 diabetes or type 2 diabetes [see Clinical Studies (14)].

The data in Table 1 reflect the exposure of 596 patients with type 1 diabetes to insulin aspart in one clinical trial with a mean exposure duration to insulin aspart of 24 weeks. The mean age was 39 years. Fifty-one percent were male, 94% were Caucasian, 2% were Black and 4% were other races. The mean body mass index (BMI) was 25.6 kg/m^2. The mean duration of diabetes was 15.7 years and the mean HbA1c at baseline was 7.9%.

The data in Table 2 reflect the exposure of 91 patients with type 2 diabetes to insulin aspart in one clinical trial with a mean exposure duration to insulin aspart of 24 weeks. The mean age was 57 years. Sixty-three percent were male, 76% were Caucasian, 9% were Black and 15% were other races. The mean BMI was 29.7 kg/m^2. The mean duration of diabetes was 12.7 years and the mean HbA1c at baseline was 8.1%.

Common adverse reactions were defined as events that occurred in ≥5%, excluding hypoglycemia, of the population studied. Common adverse events that occurred at the same rate or greater for insulin aspart-treated patients than in comparator-treated patients during clinical trials in patients with type 1 diabetes mellitus and type 2 diabetes mellitus (other than hypoglycemia) are listed in Table 1 and Table 2, respectively.

Table 1: Adverse reactions that occurred in ≥5% of Type 1 Diabetes Mellitus Adult Patients treated with insulin aspart and at the same rate or greater on insulin aspart than on comparator
 | Insulin aspart + NPH (%) (n= 596) | Regular Human Insulin + NPH (%) (n= 286)
Headache | 12 | 10
Injury accidental | 11 | 10
Nausea | 7 | 5
Diarrhea | 5 | 3

Table 2: Adverse reactions that occurred in ≥5% of Type 2 Diabetes Mellitus Adult Patients treated with insulin aspart and at the same rate or greater on insulin aspart than on comparator
 | Insulin aspart + NPH (%) (n= 91) | Human Regular Insulin + NPH (%) (n= 91)
Hyporeflexia | 11 | 7
Onychomycosis | 10 | 5
Sensory disturbance | 9 | 7
Urinary tract infection | 8 | 7
Chest pain | 5 | 3
Headache | 5 | 3
Skin disorder | 5 | 2
Abdominal pain | 5 | 1
Sinusitis | 5 | 1

Severe Hypoglycemia

Hypoglycemia is the most commonly observed adverse reaction in patients using insulin, including insulin aspart products [see Warnings and Precautions (5.3)]. The rates of reported hypoglycemia depend on the definition of hypoglycemia used, diabetes type, insulin dose, intensity of glucose control, background therapies, and other intrinsic and extrinsic patient factors. For these reasons, comparing rates of hypoglycemia in clinical trials for insulin aspart with the incidence of hypoglycemia for other products may be misleading and also, may not be representative of hypoglycemia rates that will occur in clinical practice.

Severe hypoglycemia was defined as hypoglycemia associated with central nervous system symptoms and requiring the intervention of another person or hospitalization. The incidence of severe hypoglycemia in:

- Adult and pediatric patients with type 1 diabetes mellitus who received subcutaneous insulin aspart was 17% at 24 weeks and 6% at 24 weeks, respectively [see Clinical Studies (14)].
- Adult patients with type 2 diabetes mellitus who received subcutaneous insulin aspart was 10% at 24 weeks.

Allergic Reactions

Some patients taking insulin, including insulin aspart products have experienced erythema, local edema, and pruritus at the site of injection. These conditions were usually self-limiting. Severe cases of generalized allergy (anaphylaxis) have been reported.

Adverse Reactions Associated with Insulin Initiation and Glucose Control Intensification

Intensification or rapid improvement in glucose control has been associated with a transitory, reversible ophthalmologic refraction disorder, worsening of diabetic retinopathy, and acute painful peripheral neuropathy. However, long-term glycemic control decreases the risk of diabetic retinopathy and neuropathy.

Lipodystrophy

Administration of insulin, including insulin aspart products subcutaneously, has resulted in lipoatrophy (depression in the skin) or lipohypertrophy (enlargement or thickening of tissue) in some patients [see Dosage and Administration (2.2)].

Peripheral Edema

Insulins, including insulin aspart products, may cause sodium retention and edema, particularly if previously poor metabolic control is improved by intensified insulin therapy.

Weight Gain

Weight gain has occurred with insulins, including insulin aspart products, and has been attributed to the anabolic effects of insulin and the decrease in glucosuria.

6.2 Immunogenicity

As with all therapeutic proteins, there is potential for immunogenicity. The detection of antibody formation is highly dependent on the sensitivity and specificity of the assay. Additionally, the observed incidence of antibody (including neutralizing antibody) positivity in an assay may be influenced by several factors including assay methodology, sample handling, timing of sample collection, concomitant medications, and underlying disease. For these reasons, comparison of the incidence of antibodies in the studies described below with the incidence of antibodies in other studies or to other insulin aspart products may be misleading.

In a 6-month study with a 6-month extension in adult subjects with type 1 diabetes, 99.8% of patients who received insulin aspart were positive for anti-insulin antibodies (AIA) at least once during the study, including 97.2% that were positive at baseline. A total of 92.1% of patients who received insulin aspart were positive for anti-drug antibodies (ADA) at least once during the study, including 64.6% that were positive at baseline.

In a phase 3 type 1 diabetes clinical trial of insulin aspart, initial increase in titers of antibodies to insulin, followed by a decrease to baseline values, was observed in regular human insulin and insulin aspart treatment groups with similar incidences. These antibodies did not cause deterioration in glycemic control or necessitate increases in insulin dose.

6.3 Postmarketing Experience

The following adverse reactions have been identified during post-approval use of insulin aspart products. Because these adverse reactions are reported voluntarily from a population of uncertain size, it is generally not possible to reliably estimate their frequency or establish a causal relationship to drug exposure.

Medication errors have been reported in which other insulins have been accidentally substituted for insulin aspart products.

Localized cutaneous amyloidosis at the injection site has occurred with insulin aspart products. Hyperglycemia has been reported with repeated insulin injections into areas of localized cutaneous amyloidosis; hypoglycemia has been reported with a sudden change to an unaffected injection site.

7 DRUG INTERACTIONS

The table below presents clinically significant drug interactions with MERILOG.

Drugs That May Increase the Risk of Hypoglycemia
Drugs: | Antidiabetic agents, ACE inhibitors, angiotensin II receptor blocking agents, disopyramide, fibrates, fluoxetine, monoamine oxidase inhibitors, pentoxifylline, pramlintide, salicylates, somatostatin analog (e.g., octreotide), and sulfonamide antibiotics.
Intervention: | Dose adjustment and increased frequency of glucose monitoring may be required when MERILOG is concomitantly administered with these drugs.
Drugs That May Decrease the Blood Glucose Lowering Effect of MERILOG
Drugs: | Atypical antipsychotics (e.g., olanzapine and clozapine), corticosteroids, danazol, diuretics, estrogens, glucagon, isoniazid, niacin, oral contraceptives, phenothiazines, progestogens (e.g., in oral contraceptives), protease inhibitors, somatropin, sympathomimetic agents (e.g., albuterol, epinephrine, terbutaline), and thyroid hormones.
Intervention: | Dose adjustment and increased frequency of glucose monitoring may be required when MERILOG is concomitantly administered with these drugs.
Drugs That May Increase or Decrease the Blood Glucose Lowering Effect of MERILOG
Drugs: | Alcohol, beta-blockers, clonidine, and lithium salts. Pentamidine may cause hypoglycemia, which may sometimes be followed by hyperglycemia. Pentamidine may cause hypoglycemia, which may sometimes be followed by hyperglycemia.
Intervention: | Dose adjustment and increased frequency of glucose monitoring may be required when MERILOG is concomitantly administered with these drugs.
Drugs That May Blunt Signs and Symptoms of Hypoglycemia
Drugs: | Beta-blockers, clonidine, guanethidine and reserpine
Intervention: | Increased frequency of glucose monitoring may be required when MERILOG is concomitantly administered with these drugs.

8 USE IN SPECIFIC POPULATIONS

8.1 Pregnancy

Risk Summary

Available information from published randomized controlled trials with insulin aspart products use during the second trimester of pregnancy have not reported an association with insulin aspart products and major birth defects or adverse maternal or fetal outcomes [see Data]. There are risks to the mother and fetus associated with poorly controlled diabetes in pregnancy [see Clinical Considerations].

In animal reproduction studies, administration of subcutaneous insulin aspart to pregnant rats and rabbits during the period of organogenesis did not cause adverse developmental effects at exposures 8-times and equal to the human subcutaneous dose of 1 unit/kg/day, respectively. Pre- and post-implantation losses and visceral/skeletal abnormalities were seen at higher exposures, which are considered secondary to maternal hypoglycemia. These effects were similar to those observed in rats administered regular human insulin [see Data].

In the U.S. general population, the estimated background risk of major birth defects and miscarriage in clinically recognized pregnancies is 2 to 4% and 15 to 20%, respectively. The estimated background risk of major birth defects is 6 to 10% in women with pre-gestational diabetes with a periconceptual HbA1c >7% and has been reported to be as high as 20 to 25% in women with a periconceptual HbA1c >10%. The estimated background risk of miscarriage for the indicated population is unknown.

Clinical Considerations

Disease-Associated Maternal and/or Embryo-Fetal Risk

Poorly controlled diabetes in pregnancy increases the maternal risk for diabetic ketoacidosis, preeclampsia, spontaneous abortions, preterm delivery, and delivery complications. Poorly controlled diabetes increases the fetal risk for major birth defects, stillbirth, and macrosomia related morbidity.

Data

Human Data

Published data from 5 randomized controlled trials of 441 pregnant women with diabetes mellitus treated with insulin aspart products during the late 2nd trimester of pregnancy did not identify an association of insulin aspart products with major birth defects or adverse maternal or fetal outcomes. However, these studies cannot definitely establish the absence of any risk because of methodological limitations, including a variable duration of treatment and small size of the majority of the trials.

Animal Data

Fertility, embryo-fetal and pre- and postnatal development studies have been performed with insulin aspart and regular human insulin in rats and rabbits. In a combined fertility and embryo-fetal development study in rats, insulin aspart was administered before mating, during mating, and throughout pregnancy. Further, in a pre- and postnatal development study insulin aspart was given throughout pregnancy and during lactation to rats. In an embryo-fetal development study insulin aspart was given to female rabbits during organogenesis. The effects of insulin aspart did not differ from those observed with subcutaneous regular human insulin. Insulin aspart, like human insulin, caused pre- and post-implantation losses and visceral/skeletal abnormalities in rats at a dose of 200 units/kg/day (approximately 32 times the human subcutaneous dose of 1 unit/kg/day, based on human exposure equivalents) and in rabbits at a dose of 10 units/kg/day (approximately three times the human subcutaneous dose of 1 unit/kg/day, based on human exposure equivalents). No significant effects were observed in rats at a dose of 50 units/kg/day and in rabbits at a dose of 3 units/kg/day. These doses are approximately 8 times the human subcutaneous dose of 1 unit/kg/day for rats and equal to the human subcutaneous dose of 1 unit/kg/day for rabbits, based on human exposure equivalents. The effects are considered secondary to maternal hypoglycemia.

8.2 Lactation

Risk Summary

There are no data on the presence of insulin aspart products in human milk, the effects on the breastfed infant, or the effect on milk production. One small published study reported that exogenous insulin, including insulin aspart, was present in human milk. However, there is insufficient information to determine the effects of insulin aspart products on the breastfed infant. The developmental and health benefits of breastfeeding should be considered along with the mother's clinical need for MERILOG, and any potential adverse effects on the breastfed infant from MERILOG, or from the underlying maternal condition.

8.4 Pediatric Use

The safety and effectiveness of MERILOG to improve glycemic control have been established in pediatric patients with diabetes mellitus. Use of MERILOG for this indication is supported by evidence from an adequate and well-controlled study of insulin aspart in 283 pediatric patients with type 1 diabetes mellitus aged 6 to 18 years and from studies in adults with diabetes mellitus [see Adverse Reactions (6.1), Clinical Pharmacology (12.3), and Clinical Studies (14)].

8.5 Geriatric Use

Of the total number of patients (n=1,375) treated with insulin aspart in 3 controlled clinical studies, 2.6% (n=36) were 65 years of age or over. One-half of these patients had type 1 diabetes (18/1285) and the other half had type 2 diabetes (18/90). The HbA1c response to insulin aspart, as compared to regular human insulin, did not differ by age.

8.6 Renal Impairment

Patients with renal impairment may be at increased risk of hypoglycemia and may require more frequent MERILOG dose adjustment and more frequent blood glucose monitoring [see Warnings and Precautions (5.3) and Clinical Pharmacology (12.3)].

8.7 Hepatic Impairment

Patients with hepatic impairment may be at increased risk of hypoglycemia and may require more frequent MERILOG dose adjustment and more frequent blood glucose monitoring [see Warnings and Precautions (5.3) and Clinical Pharmacology (12.3)].

10 OVERDOSAGE

Excess insulin administration may cause hypoglycemia and hypokalemia [see Warnings and Precautions (5.3, 5.6)]. Mild episodes of hypoglycemia usually can be treated with oral glucose. Adjustments in drug dosage, meal patterns, or exercise may be needed. More severe episodes with coma, seizure, or neurologic impairment may be treated with intramuscular/subcutaneous glucagon or concentrated intravenous glucose. Sustained carbohydrate intake and observation may be necessary because hypoglycemia may recur after apparent clinical recovery. Hypokalemia must be corrected appropriately.

11 DESCRIPTION

Insulin aspart-szjj is a rapid-acting human insulin analog homologous with regular human insulin with the exception of a single substitution of the amino acid proline by aspartic acid in position B28, and is produced by recombinant DNA technology utilizing Escherichia coli. Insulin aspart-szjj has a molecular weight of 5825.8 Da.

MERILOG (insulin aspart-szjj) injection is a sterile, clear, and colorless solution for subcutaneous use. Each mL contains 100 units of insulin aspart-szjj and the inactive ingredients: 1.72 mg metacresol, 1.50 mg phenol, 0.02 mg polysorbate 20, 6.80 mg sodium chloride, 0.04 mg zinc chloride and Water for Injection, USP. MERILOG has a pH of 7.0–7.8. Hydrochloric acid and/or sodium hydroxide may be added to adjust pH.

12 CLINICAL PHARMACOLOGY

12.1 Mechanism of Action

The primary activity of insulin, including insulin aspart products is the regulation of glucose metabolism. Insulin and its analogs lower blood glucose by stimulating peripheral glucose uptake, especially by skeletal muscle and fat, and by inhibiting hepatic glucose production. Insulin inhibits lipolysis and proteolysis, and enhances protein synthesis.

12.2 Pharmacodynamics

Pharmacodynamics of Insulin Aspart After Subcutaneous Administration

The pharmacodynamic profile of insulin aspart given subcutaneously in 22 patients with type 1 diabetes is shown in Figure 1. The maximum glucose-lowering effect of insulin aspart occurred between 1 and 3 hours after subcutaneous injection (0.15 units/kg). The duration of action for insulin aspart is 3 to 5 hours. The time course of action of insulin and insulin analogs such as insulin aspart products may vary considerably in different individuals or within the same individual. The parameters of insulin aspart activity (time of onset, peak time and duration) as designated in Figure 1 should be considered only as general guidelines. The rate of insulin absorption and onset of activity is affected by the site of injection, exercise, and other variables [see Warnings and Precautions (5.3)].

Figure 1. Serial mean serum glucose collected up to 6 hours following a single 0.15 units/kg pre-meal dose of insulin aspart (solid curve) or regular human insulin (hatched curve) injected immediately before a meal in 22 patients with type 1 diabetes.

12.3 Pharmacokinetics

Pharmacokinetics of subcutaneous administration of insulin aspart is presented below.

Absorption and Bioavailability

In studies in healthy volunteers (total n=107) and patients with type 1 diabetes (total n=40), the median time to maximum concentration of insulin aspart in these trials was 40 to 50 minutes versus 80 to 120 minutes, for regular human insulin respectively.

The relative bioavailability of insulin aspart (0.15 units/kg) compared to regular human insulin indicates that the two insulins are absorbed to a similar extent.

In a clinical trial in patients with type 1 diabetes, insulin aspart and regular human insulin, both administered subcutaneously at a dose of 0.15 units/kg body weight, reached mean maximum concentrations of 82 and 36 mU/L, respectively.

Distribution

Insulin aspart has a low binding affinity to plasma proteins (<10%), similar to that seen with regular human insulin.

Figure 2. Serial mean serum free insulin concentration collected up to 6 hours following a single 0.15 units/kg pre-meal dose of insulin aspart (solid curve) or regular human insulin (hatched curve) injected immediately before a meal in 22 patients with type 1 diabetes.

Metabolism and Elimination

After subcutaneous administration in normal male volunteers (n=24), insulin aspart was eliminated with an average apparent half-life of 81 minutes.

Specific Populations

Pediatric Patients: The pharmacokinetic and pharmacodynamic properties of insulin aspart and regular human insulin were evaluated in a single dose study in 18 pediatric patients with type 1 diabetes in 2 age groups: 6–12 years, n=9 and 13–17 years (Tanner grade ≥2), n=9. The relative differences in pharmacokinetics and pharmacodynamics in the pediatric patients with type 1 diabetes in both age groups between insulin aspart and regular human insulin were similar to those in healthy adult subjects and adults with type 1 diabetes.

Geriatric Patients: The pharmacokinetic and pharmacodynamic properties of insulin aspart and regular human insulin were investigated in a single dose study in 18 subjects with type 2 diabetes who were ≥65 years of age. The relative differences in pharmacokinetics and pharmacodynamics in geriatric patients with type 2 diabetes between insulin aspart and regular human insulin were similar to those in younger adults.

Male and Female Patients: In healthy volunteers given a single subcutaneous dose of insulin aspart 0.06 units/kg, no difference in insulin aspart levels was seen between males and females based on comparison of AUC(0–10h) or Cmax.

Obese Patients: A single subcutaneous dose of 0.1 units/kg insulin aspart was administered in a study of 23 patients with type 1 diabetes and a wide range of body mass index (BMI, 22–39 kg/m^2). The pharmacokinetic parameters, AUC and Cmax, of insulin aspart were generally unaffected by BMI in the different groups – BMI 19–23 kg/m^2 (n=4); BMI 23–27 kg/m^2 (n=7); BMI 27–32 kg/m^2 (n=6) and BMI >32 kg/m^2 (n=6). Clearance of insulin aspart was reduced by 28% in patients with BMI >32 kg/m^2 compared to patients with BMI <23 kg/m^2.

Patients with Renal Impairment: A single subcutaneous dose of 0.08 units/kg insulin aspart was administered in a study to subjects with either normal renal function (n=6) creatinine clearance (CLcr) (>80 ml/min) or mild (n=7; CLcr=50–80 ml/min), moderate (n=3; CLcr=30–50 ml/min) or severe (but not requiring hemodialysis) (n=2; CLcr = <30 ml/min) renal impairment. In this study, there was no apparent effect of creatinine clearance values on AUC and Cmax of insulin aspart.

Patients with Hepatic Impairment: A single subcutaneous dose of 0.06 units/kg insulin aspart was administered in an open-label, single-dose study of 24 subjects (n=6/group) with different degree of hepatic impairment (mild, moderate and severe) having Child-Pugh Scores ranging from 0 (healthy volunteers) to 12 (severe hepatic impairment). In this study, there was no correlation between the degree of hepatic impairment and any insulin aspart pharmacokinetic parameter.

13 NONCLINICAL TOXICOLOGY

13.1 Carcinogenesis, Mutagenesis, Impairment of Fertility

Standard 2-year carcinogenicity studies in animals have not been performed to evaluate the carcinogenic potential of insulin aspart products. In 52-week studies, Sprague-Dawley rats were dosed subcutaneously with insulin aspart at 10, 50, and 200 units/kg/day (approximately 2, 8, and 32 times the human subcutaneous dose of 1.0 units/kg/day, based on units/body surface area, respectively). At a dose of 200 units/kg/day, insulin aspart increased the incidence of mammary gland tumors in females when compared to untreated controls. The relevance of these findings to humans is unknown.

Insulin aspart was not genotoxic in the following tests: Ames test, mouse lymphoma cell forward gene mutation test, human peripheral blood lymphocyte chromosome aberration test, in vivo micronucleus test in mice, and in ex vivo UDS test in rat liver hepatocytes.

In fertility studies in male and female rats, at subcutaneous doses up to 200 units/kg/day (approximately 32 times the human subcutaneous dose, based on units/body surface area), no direct adverse effects on male and female fertility, or general reproductive performance of animals was observed.

13.2 Animal Toxicology and/or Pharmacology

In standard biological assays in mice and rabbits, one unit of insulin aspart has the same glucose-lowering effect as one unit of regular human insulin.

14 CLINICAL STUDIES

14.1 Overview of Clinical Studies

The safety and effectiveness of subcutaneous insulin aspart were compared to regular human insulin in 596 type 1 diabetes adult, 187 pediatric type 1 diabetes, and 91 adult type 2 diabetes patients using NPH as basal insulin (see Tables 3, 4, 5). The reduction in glycated hemoglobin (HbA1c) was similar to regular human insulin.

14.2 Clinical Studies in Adult and Pediatric Patients with Type 1 Diabetes with Subcutaneous Injections

Type 1 Diabetes - Adults (see Table 3)

Two 24-week, open-label, active-controlled studies were conducted to compare the safety and efficacy of insulin aspart to regular human insulin injection in adult patients with type 1 diabetes. Because the two study designs and results were similar, data are shown for only one study (see Table 3).

The mean age of the trial population was 39 years and mean duration of diabetes was 15.7 years. Fifty-one percent were male. Ninety-four percent were Caucasian, 2% were Black and 4% were Other. The mean BMI was approximately 25.6 kg/m^2.

Insulin aspart was administered by subcutaneous injection immediately prior to meals and regular human insulin was administered by subcutaneous injection 30 minutes before meals. NPH insulin was administered as the basal insulin in either single or divided daily doses. Changes in HbA1c were comparable for the two treatment regimens in this study (Table 3).

Table 3. Type 1 Diabetes Mellitus – Adult (insulin aspart plus NPH insulin vs. regular human insulin plus NPH insulin)
 | Insulin aspart + NPH (n=596) | Regular Human Insulin + NPH (n=286)
Baseline HbA1c (%) [Values are Mean ± SD] | 7.9 ± 1.1 | 8.0 ± 1.2
Change from Baseline HbA1c (%) | -0.1 ± 0.8 | 0.0 ± 0.8
Treatment Difference in HbA1c, Mean (95% confidence interval) | -0.2 (-0.3, -0.1)

Type 1 Diabetes – Pediatric (see Table 4)

The efficacy of insulin aspart to improve glycemic control in pediatric patients with type 1 diabetes mellitus is based on an adequate and well-controlled trial of regular human insulin in pediatric patients with type 1 diabetes mellitus (Table 4). This 24-week, parallel-group study of pediatric patients with type 1 diabetes (n=283), aged 6 to 18 years, compared two subcutaneous multiple-dose treatment regimens: insulin aspart (n=187) or regular human insulin (n=96). NPH insulin was administered as the basal insulin. Similar effects on HbA1c were observed in both treatment groups (Table 4).

Subcutaneous administration of insulin aspart and regular human insulin have also been compared in pediatric patients with type 1 diabetes (n=26) aged 2 to 6 years with similar effects on HbA1c.

Table 4. Pediatric Subcutaneous Administration of Insulin Aspart in Type 1 Diabetes (24 weeks; n=283)
 | Insulin aspart + NPH (n=187) | Regular Human Insulin + NPH (n=96)
Baseline HbA1c (%) [Values are Mean ± SD] | 8.3 ± 1.2 | 8.3 ± 1.3
Change from Baseline HbA1c (%) | 0.1 ± 1.0 | 0.1 ± 1.1
Treatment Difference in HbA1c, Mean (95% confidence interval) | -0.2 (-0.5, 0.1)

14.3 Clinical Studies in Adults with Type 2 Diabetes with Subcutaneous Injections

Type 2 Diabetes - Adults (see Table 5)

One six-month, open-label, active-controlled study was conducted to compare the safety and efficacy of insulin aspart to regular human insulin in patients with type 2 diabetes (Table 5).

The mean age of the trial population was 56.6 years and mean duration of diabetes was 12.7 years. Sixty-three percent were male. Seventy-six percent were Caucasian, 9% were Black and 15% were Other. The mean BMI was approximately 29.7 kg/m^2.

Insulin aspart was administered by subcutaneous injection immediately prior to meals and regular human insulin was administered by subcutaneous injection 30 minutes before meals. NPH insulin was administered as the basal insulin in either single or divided daily doses. Changes in HbA1c were comparable for the two treatment regimens.

Table 5. Subcutaneous Insulin Aspart Administration in Type 2 Diabetes (6 months; n=176)
 | Insulin aspart + NPH (n=90) | Regular Human Insulin + NPH (n=86)
Baseline HbA1c (%) [Values are Mean ± SD] | 8.1 ± 1.2 | 7.8 ± 1.1
Change from Baseline HbA1c (%) | -0.3 ± 1.0 | -0.1 ± 0.8
Treatment Difference in HbA1c, Mean (95% confidence interval) | -0.1 (-0.4, 0.1)

16 HOW SUPPLIED/STORAGE AND HANDLING

16.1 How Supplied

MERILOG (insulin aspart-szjj) injection 100 units/mL (U-100) is available as a clear and colorless solution in:

Dosage Unit | NDC #
One 10 mL multiple-dose vial per carton | NDC 0024-5927-00
Five 3 mL single-patient-use SoloStar prefilled pens per carton | NDC 0024-5928-05

The MERILOG SoloStar prefilled pen dials in 1-unit increments.

Needles are not included in MERILOG SoloStar packs. Only use needles that are compatible for use with MERILOG SoloStar which are sold separately, including needles from Becton, Dickinson and company (BD) (such as BD Ultra-Fine®), Ypsomed (such as Clickfine®), and Owen Mumford (such as Unifine® Pentips®).

16.2 Recommended Storage

Dispense in the original sealed carton with the enclosed Instructions for Use.

Store unused MERILOG in a refrigerator between 2°C to 8°C (36°F to 46°F). Do not freeze MERILOG and do not use MERILOG if it has been frozen. Do not expose MERILOG to excessive heat or light.

Do not withdraw MERILOG into a syringe and store for later use.

Always remove and discard the needle after each injection from the MERILOG SoloStar prefilled pen and store without a needle attached.

The storage conditions are summarized in the following table:

Table 6. Storage Conditions for Vial and SoloStar Prefilled Pen
MERILOG presentation | Not in-use (unopened) Room Temperature (up to 30°C [86°F]) | Not in-use (unopened) Refrigerated (2°C to 8°C [36°F to 46°F]) | In-use (opened) Room Temperature (up to 30°C [86°F])
10 mL multiple-dose vial | 28 days | Until expiration date | 28 days (refrigerated/room temperature)
3 mL single-patient-use SoloStar prefilled pen | 28 days | Until expiration date | 28 days (Do not refrigerate)

17 PATIENT COUNSELING INFORMATION

Advise the patient to read the FDA-approved patient labeling (Patient Information and Instructions for Use).

Never Share a MERILOG SoloStar Prefilled Pen between Patients

Advise patients that they must never share MERILOG SoloStar prefilled pen device with another person even if the needle is changed, because doing so carries a risk for transmission of blood-borne pathogens. Advise patients using MERILOG vials not to share needles or syringes with another person. Sharing poses a risk for transmission of blood-borne pathogens [see Warnings and Precautions (5.1)].

Hyperglycemia or Hypoglycemia

Inform patients that hypoglycemia is the most common adverse reaction with insulin. Instruct patients on self-management procedures including glucose monitoring, proper injection technique, and management of hypoglycemia and hyperglycemia, especially at initiation of MERILOG therapy. Instruct patients on handling of special situations such as intercurrent conditions (illness, stress, or emotional disturbances), an inadequate or skipped insulin dose, inadvertent administration of an increased insulin dose, inadequate food intake, and skipped meals. Instruct patients on the management of hypoglycemia [see Warnings and Precautions (5.3)].

Inform patients that their ability to concentrate and react may be impaired as a result of hypoglycemia. Advise patients who have frequent hypoglycemia or reduced or absent warning signs of hypoglycemia to use caution when driving or operating machinery.

Advise patients that changes in insulin regimen can predispose to hyperglycemia or hypoglycemia and that changes in insulin regimen should be made under close medical supervision [see Warnings and Precautions (5.2)].

Hypoglycemia with Medication Errors

Instruct patients to always check the insulin label before each injection to avoid mix-ups between insulin products [see Warnings and Precautions (5.4)].

Hypersensitivity Reactions

Advise patients that hypersensitivity reactions have occurred with insulin aspart products. Inform patients of the symptoms of hypersensitivity reactions [see Warnings and Precautions (5.5)].

Manufactured by:
sanofi-aventis U.S. LLC
Morristown, NJ 07960
A SANOFI COMPANY
U.S. License No. 1752

©2025 Sanofi. All rights reserved.
All trademarks mentioned in this document are the property of the Sanofi group with the exception of Novolog, BD Ultra-Fine, Clickfine, Unifine, and Pentips.

PATIENT INFORMATION
MERILOG™ [mer-ih-lawg]
(insulin aspart-szjj)
injection, for subcutaneous use
100 units/mL (U-100)

Do not share your MERILOG SoloStar prefilled pen with other people, even if the needle has been changed. You may give other people a serious infection, or get a serious infection from them.

What is MERILOG?

- MERILOG is a man-made insulin that is used to control high blood sugar in adults and children with diabetes mellitus.

Who should not take MERILOG?
Do not take MERILOG if you:

- are having an episode of low blood sugar (hypoglycemia).
- have an allergy to insulin aspart products or any of the ingredients in MERILOG.

Before taking MERILOG, tell your healthcare provider about all your medical conditions including, if you are:

- pregnant, planning to become pregnant, or are breastfeeding.
- taking new prescription or over-the-counter medicines, vitamins, or herbal supplements.

Before you start taking MERILOG, talk to your healthcare provider about low blood sugar and how to manage it.

How should I take MERILOG?

- Read the Instructions for Use that come with your MERILOG.
- Take MERILOG exactly as your healthcare provider tells you to.
- MERILOG starts acting fast. You should eat a meal within 5 to 10 minutes after you take your dose of MERILOG.
- Know the type and strength of insulin you take. Do not change the type of insulin you take unless your healthcare provider tells you to. The amount of insulin and the best time for you to take your insulin may need to change if you take different types of insulin.
- Check your blood sugar levels. Ask your healthcare provider what your blood sugars should be and when you should check your blood sugar levels.
- Do not reuse or share your needles with other people. You may give other people a serious infection or get a serious infection from them.
- MERILOG can be injected under the skin (subcutaneously) of your stomach area (abdomen), buttocks, upper legs (thighs), or upper arms.
- Change (rotate) your injection sites within the area you choose with each dose to reduce your risk of getting pits in skin or thickened skin (lipodystrophy) and skin with lumps (localized cutaneous amyloidosis) at the injection sites.
  - Do not use the exact same spot for each injection.
  - Do not inject where the skin has pits, is thickened, or has lumps.
  - Do not inject where the skin is tender, bruised, scaly or hard, or into scars or damaged skin.

What should I avoid while taking MERILOG?
While taking MERILOG do not:

- Drive or operate heavy machinery, until you know how MERILOG affects you.
- Drink alcohol or use prescription or over-the-counter medicines that contain alcohol.

What are the possible side effects of MERILOG?
MERILOG can cause serious side effects that can lead to death, including:
Low blood sugar (hypoglycemia). Signs and symptoms that may indicate low blood sugar include:

- dizziness or light-headedness
- sweating
- confusion
- fast heart beat

- blurred vision
- slurred speech
- shakiness

- anxiety, irritability, or mood changes
- hunger
- headache

Your insulin dose may need to change because of:

- change in level of physical activity or exercise
- weight gain or loss

- increased stress
- illness

- change in diet

Other common side effects of MERILOG may include:

- low potassium in your blood (hypokalemia), reactions at the injection site, itching, rash, serious allergic reactions (whole body reactions), skin thickening or pits at the injection site (lipodystrophy), weight gain, and swelling of your hands and feet.

Get emergency medical help if you have:

- trouble breathing, shortness of breath, fast heartbeat, swelling of your face, tongue, or throat, sweating, extreme drowsiness, dizziness, confusion.

These are not all the possible side effects of MERILOG. Call your doctor for medical advice about side effects. You may report side effects to FDA at 1-800-FDA-1088.

General information about the safe and effective use of MERILOG.
Medicines are sometimes prescribed for purposes other than those listed in a Patient Information leaflet. You can ask your pharmacist or healthcare provider for information about MERILOG that is written for health professionals. Do not use MERILOG for a condition for which it was not prescribed. Do not give MERILOG to other people, even if they have the same symptoms that you have. It may harm them.

What are the ingredients in MERILOG?
Active Ingredient: insulin aspart-szjj
Inactive Ingredients: metacresol, phenol, polysorbate 20, sodium chloride, zinc chloride and Water for Injection, USP. Hydrochloric acid and/or sodium hydroxide may be added to adjust pH.
Manufactured by: sanofi-aventis U.S. LLC, Morristown, NJ 07960, A SANOFI COMPANY. U.S. License No. 1752
For more information, go to www.sanofi.com or call 1-800-633-1610.
©2025 Sanofi. All rights reserved.
All trademarks mentioned in this document are the property of the Sanofi group.

This Patient Information has been approved by the U.S. Food and Drug Administration.

Issued: May 2025

INSTRUCTIONS FOR USE MERILOG™ [mer-ih-lawg] (insulin aspart-szjj) injection, for subcutaneous use 10 mL multiple-dose vial: 100 units/mL (U-100)

This Instructions for Use contains information on how to inject MERILOG.

Read this Instructions for Use before you start taking MERILOG and each time you get a new MERILOG vial. There may be new information. This information does not take the place of talking to your healthcare provider about your medical condition or your treatment.

Do not share your MERILOG syringes with other people, even if the needle has been changed. You may give other people a serious infection, or get a serious infection from them.

Supplies needed to give your injection

- a MERILOG 10 mL vial
- a U-100 insulin syringe and needle
- 2 alcohol swabs
- 1 sharps container for throwing away used needles and syringes. See "Disposing of used needles and syringes" at the end of these instructions.

Preparing your MERILOG dose

- Wash your hands with soap and water or with alcohol.
- Check the MERILOG label to make sure you are taking the right type of insulin. This is especially important if you use more than 1 type of insulin.
- Check that the insulin is clear and colorless. Do not use the vial if the insulin looks cloudy, colored or contains particles.
- Do not use MERILOG after the expiration date stamped on the label or 28 days after you first use it.
- Always use a syringe that is marked for U-100 insulin. If you use a syringe other than a U-100 insulin syringe, you may get the wrong dose of insulin.
- Always use a new syringe or needle for each injection to help maintain sterility and prevent blocked needles. Do not reuse or share your syringes or needles with other people. You may give other people a serious infection or get a serious infection from them.

Need help?

If you have any questions about your vial or about diabetes, ask your healthcare provider, or call sanofi-aventis at 1-800-633-1610.

Step 1:

If you are using a new vial, remove the protective cap. Do not remove the stopper (see Figure A).

(Figure A)

Step 2:

Wipe the top of the vial with an alcohol swab. You do not have to shake the vial of MERILOG before use (see Figure B).

(Figure B)

Step 3:

Draw air into the syringe equal to your insulin dose (see Figure C). Put the needle through the rubber top of the vial and push the plunger to inject the air into the vial (see Figure D).

(Figure C)

(Figure D)

Step 4:

Leave the syringe in the vial and turn both upside down. Hold the syringe and vial firmly in one hand. Make sure the tip of the needle is in the insulin. With your free hand, pull the plunger to withdraw the correct dose into the syringe (see Figure E).

(Figure E)

Step 5:

Before you take the needle out of the vial, check the syringe for air bubbles. If bubbles are in the syringe, hold the syringe straight up and tap the side of the syringe until the bubbles float to the top. Push the bubbles out with the plunger and draw insulin back in until you have the correct dose (see Figure F).

(Figure F)

Step 6:

Remove the needle from the vial. Do not let the needle touch anything. You are now ready to inject.

Giving your MERILOG injection with a syringe

- Inject your insulin exactly as your healthcare provider has shown you.
- MERILOG starts acting fast. You should eat a meal within 5 to 10 minutes after you take your dose of MERILOG.

Step 7:

- Choose your injection site: MERILOG is injected under the skin (subcutaneously) of your stomach area (abdomen), buttocks, upper legs (thighs) or upper arms (see Figure G).
- Do not use the exact same spot for each injection. Change (rotate) your injection sites within the area you choose for each dose to reduce your risk of getting pits in the skin or thickened skin (lipodystrophy) and skin with lumps (localized cutaneous amyloidosis) at the injection sites.
- Do not inject where the skin has pits, is thickened, or has lumps.
- Do not inject where the skin is tender, bruised, scaly or hard, or into scars or damaged skin.
  (Figure G)
- Wipe the skin with an alcohol swab to clean the injection site. Let the injection site dry before you inject your dose (see Figure H).
  (Figure H)

Step 8:

- Pinch the skin.
- Insert the needle in the way your healthcare provider showed you.
- Release the skin.
- Slowly push in the plunger of the syringe all the way, making sure you have injected all the insulin.
- Leave the needle in the skin for about 10 seconds (see Figure I).
  (Figure I)

Step 9:

- Pull the needle straight out of your skin.
- Gently press the injection site for several seconds. Do not rub the area.
- Do not recap the used needle. Recapping the needle can lead to a needle-stick injury.

Disposing of used needles and syringes

- Put your used needles and syringes in a FDA-cleared sharps disposal container right away after use. Do not throw away (dispose of) loose needles and syringes in your household trash.
- If you do not have a FDA-cleared sharps container, you may use a household container that is:
  - made of a heavy-duty plastic,
  - can be closed with a tight-fitting, puncture-resistant lid, without sharps being able to come out,
  - upright and stable during use,
  - leak resistant, and
  - properly labeled to warn of hazardous waste inside the container.
- When your sharps disposal container is almost full, you will need to follow your community guidelines for the right way to dispose of your sharps disposal container. There may be state or local laws about how you should throw away used needles and syringes. For more information about safe sharps disposal, and for specific information about sharps disposal in the state that you live in, go to the FDA's website at: http://www.fda.gov/safesharpsdisposal.
- Do not dispose of your used sharps disposal container in your household trash unless your community guidelines permit this. Do not recycle your used sharps disposal container.

How should I store MERILOG?

Unopened (not in-use) MERILOG vials

- Store unused MERILOG vials in the refrigerator between 36°F to 46°F (2°C to 8°C).
- Do not freeze MERILOG.
- Keep MERILOG away from direct heat and light.
- If a vial has been frozen or overheated, throw it away.
- Unopened vials can be used until the expiration date on the carton and label if they have been stored in the refrigerator.
- Unopened vials should be thrown away after 28 days if they are stored at room temperature.

After MERILOG vials have been opened (in-use)

- Store in-use (opened) MERILOG vials in a refrigerator between 36°F to 46°F (2°C to 8°C) or at room temperature below 86°F (30°C) for up to 28 days.
- Do not freeze MERILOG.
- Do not expose MERILOG to excessive heat or light.
- If a vial has been frozen, throw it away.
- The MERILOG vial you are using should be thrown away after 28 days, even if it still has insulin left in it.

Manufactured by:
sanofi-aventis U.S. LLC
Morristown, NJ 07960
A SANOFI COMPANY
U.S. License No. 1752

©2025 Sanofi. All rights reserved.
All trademarks mentioned in this document are the property of the Sanofi group.

This Instructions for Use has been approved by the U.S. Food and Drug Administration.

Approved: May 2025

INSTRUCTIONS FOR USE MERILOG™ SoloStar® [mer-ih-lawg soh-loh-stahr] (insulin aspart-szjj) injection, for subcutaneous use 3 mL single-patient-use prefilled pen: 100 units/mL (U-100)

This Instructions for Use contains information on how to inject MERILOG.

Read this Instructions for Use before you start taking MERILOG and each time you get a new MERILOG SoloStar prefilled pen. There may be new information. This information does not take the place of talking to your healthcare provider about your medical condition or your treatment.

Do not share your MERILOG SoloStar prefilled pen with other people, even if the needle has been changed. You may give other people a serious infection, or get a serious infection from them.

People who are blind or have vision problems should not use MERILOG SoloStar prefilled pen without help from a person trained to use MERILOG SoloStar prefilled pen.

MERILOG SoloStar is a disposable prefilled pen used to inject MERILOG. Each MERILOG SoloStar has 300 units of insulin which can be used for multiple injections. You can select doses from 1 to 80 units in steps of 1 unit. The pen plunger moves with each dose. The plunger will only move to the end of the cartridge when 300 units of insulin have been given.

Important information

- Do not use your pen if it is damaged or if you are not sure that it is working properly.
- Do not use a syringe to remove insulin from your pen.
- Do not reuse needles. If you do, you might get the wrong dose of MERILOG or increase the chance of getting an infection.
- Always perform a safety test (see Step 3).
- Always carry a spare pen and spare needles in case they are lost or stop working.
- Change (rotate) your injection sites within the area you choose for each dose (see "Places to inject").

Learn to inject

- Talk with your healthcare provider about how to inject before using your pen.
- Ask for help if you have problems handling the pen.
- Read all of these instructions before using your pen. If you do not follow all of these instructions, you may get too much or too little insulin.

Need help?

If you have any questions about your pen or about diabetes, ask your healthcare provider, or call sanofi-aventis at 1-800-633-1610.

Extra items you will need:

- a new sterile needle (see Step 2).
- an alcohol swab.
- a puncture-resistant container for used needles and pens. (See "Throwing your pen away".)

Places to inject

- Inject your insulin exactly as your healthcare provider has shown you.
- Inject your insulin under the skin (subcutaneously) of your stomach area (abdomen), buttocks, upper legs (thighs) or upper arms (see Figure A).
- Change (rotate) your injection sites within the area you choose for each dose to reduce your risk of getting pits in skin or thickened skin (lipodystrophy) and skin with lumps (localized cutaneous amyloidosis) at the injection sites.
- Do not inject where the skin has pits, is thickened, or has lumps.
- Do not inject where the skin is tender, bruised, scaly or hard, or into scars or damaged skin.

(Figure A)

Get to know your pen

(Figure B)

Step 1: Check your pen

Take a new pen out of the refrigerator at least 1 hour before you inject. Cold insulin is more painful to inject.

1A Check the name and expiration date on the label of your pen.

- Make sure you have the correct insulin (see Figure C).
- Do not use your pen after the expiration date.
  (Figure C)

1B Pull off the pen cap (see Figure D).

(Figure D)

1C Check that the insulin is clear and colorless (see Figure E).

- Do not use the pen if the insulin looks cloudy, colored or contains particles.
  (Figure E)

1D Wipe the rubber seal with an alcohol swab (see Figure F).

(Figure F)

If you have other injector pens:

- Making sure you have the correct medicine is especially important if you have other injector pens.

Step 2: Attach a new needle

- Do not reuse needles. Always use a new sterile needle for each injection. This helps stop blocked needles, contamination, and infection.
- Only use needles* that are compatible for use with MERILOG SoloStar which are sold separately, including needles from Becton, Dickinson and company (BD) (such as BD Ultra-Fine®), Ypsomed (such as Clickfine®), and Owen Mumford (such as Unifine® Pentips®).

2A Take a new needle and peel off the protective seal (see Figure G).

(Figure G)

2B Keep the needle straight and screw it onto the pen until fixed. Do not over-tighten (see Figure H).

(Figure H)

2C Pull off the outer needle cap. Keep this for later (see Figure I).

(Figure I)

2D Pull off the inner needle cap and throw away (see Figure J).

(Figure J)

Handling needles:

- Take care when handling needles to prevent accidental needle-stick injury. You may give other people a serious infection, or get a serious infection from them (cross-infection).

Step 3: Do a safety test

Always do a safety test before each injection to:

- Check your pen and the needle to make sure they are working properly.
- Make sure that you get the correct insulin dose.

You must perform safety tests before you use the pen until you see insulin coming out of the needle tip. If you see insulin coming out of the needle tip, the pen is ready to use. If you do not see insulin coming out before taking your dose, you could get an underdose or no insulin at all. This could cause high blood sugar.

3A Select 2 units by turning the dose selector until the dose pointer is at the 2 mark (see Figure K).

(Figure K)

3B Press the injection button all the way in (see Figure L).

- When insulin comes out of the needle tip, your pen is working correctly.
  (Figure L)

If no insulin appears:

- You may need to repeat this step up to 3 times before seeing insulin.
- If no insulin comes out after the third time, the needle may be blocked. If this happens:
  - change the needle (see Step 6 and Step 2),
  - then repeat the safety test (Step 3).
- Do not use your pen if there is still no insulin coming out of the needle tip. Use a new pen.
- Do not use a syringe to remove insulin from your pen.

If you see air bubbles:

- You may see air bubbles in the insulin. This is normal, they will not harm you.

Step 4: Select the dose

Do not select a dose or press the injection button without a needle attached. This may damage your pen.

4A Make sure a needle is attached and the dose is set to "0" (see Figure M).

(Figure M)

4B Turn the dose selector until the dose pointer lines up with your dose (see Figure N).

- Always check the number in the dose window to make sure you dialed the correct dose.
- If you turn past your dose, you can turn back down.
- If there are not enough units left in your pen for your dose, the dose selector will stop at the number of units left.
- If you cannot select your full prescribed dose, use a new pen or inject the remaining units and use a new pen to complete your dose. If you use a new pen, perform a safety test (see Step 3).

(Figure N)

How to read the dose window

Even numbers are shown in line with dose pointer (see Figure O).

20 units selected
(Figure O)

Odd numbers are shown as a line between even numbers (see Figure P).

21 units selected
(Figure P)

Units of insulin in your pen:

- Your pen contains a total of 300 units of insulin. You can select doses from 1 to 80 units in steps of 1 unit. Each pen contains more than 1 dose.
- You can see roughly how many units of insulin are left by looking at where the plunger is on the insulin scale.

Step 5: Inject your dose

If you find it hard to press the injection button in, do not force it as this may break your pen. See the section after Step 5E below for help.

5A Choose a place to inject as shown in the picture labeled "Places to inject" (see Figure A). Wipe the skin with an alcohol swab to clean the injection site. Let the injection site dry before you inject your dose.

5B Push the needle into your skin as shown by your healthcare provider (see Figure Q).

- Do not touch the injection button yet.
  (Figure Q)

5C Place your thumb on the injection button. Then press all the way in and hold (see Figure R).

- Do not press at an angle. Your thumb could block the dose selector from turning.
  (Figure R)

5D Keep the injection button held in and when you see "0" in the dose window, slowly count to 10 (see Figure S).

- This will make sure you get your full dose.
  (Figure S)

5E After holding and slowly counting to 10, release the injection button. Then remove the needle from your skin.

If you find it hard to press the button in:

- Change the needle (see Step 6 and Step 2) then do a safety test (see Step 3).
- If you still find it hard to press in, get a new pen.
- Do not use a syringe to remove insulin from your pen.

Step 6: Remove the needle

- Take care when handling needles to prevent needle-stick injury and cross-infection.
- Do not put the inner needle cap back on.

6A Grip the widest part of the outer needle cap. Keep the needle straight and guide it into the outer needle cap. Then push firmly on (see Figure T).

- The needle can puncture the cap if it is recapped at an angle.
  (Figure T)

6B Grip and squeeze the widest part of the outer needle cap. Turn your pen several times with your other hand to remove the needle (see Figure U).

- Try again if the needle does not come off the first time.
  (Figure U)

6C Throw away the used needle in a puncture-resistant container (see Figure V) (see "Throwing your pen away" at the end of this Instructions for Use).

(Figure V)

6D Put your pen cap back on (see Figure W).

- Do not put the pen back in the refrigerator.
  (Figure W)

How to store your pen

Before first use

- Keep new pens in the refrigerator between 36°F to 46°F (2°C to 8°C).
- Do not freeze. Do not use MERILOG if it has been frozen.

After first use

- Keep your pen at room temperature below 86°F (30°C).
- Do not expose MERILOG to excessive heat or light.
- Store your pen with the pen cap on.
- Do not put your pen back in the refrigerator.
- Do not store your pen with the needle attached.
- Keep MERILOG SoloStar pens and needles out of the reach of children.
- Only use your pen for up to 28 days after its first use. Throw away the MERILOG SoloStar pen you are using after 28 days, even if it still has insulin left in it.

How to care for your pen

Handle your pen with care

- Do not drop your pen or knock it against hard surfaces.
- If you think that your pen may be damaged, do not try to fix it. Use a new one.

Protect your pen from dust and dirt

- You can clean the outside of your pen by wiping it with a damp cloth (water only). Do not soak, wash or lubricate your pen. This may damage it.

Throwing your pen away

- The used MERILOG SoloStar pen may be thrown away in your household trash after you have removed the needle.
- Put the used needles in a FDA-cleared sharps disposal container right away after use. Do not throw away (dispose of) loose needles in your household trash.
- If you do not have a FDA-cleared sharps disposal container, you may use a household container that is:
  - made of a heavy-duty plastic,
  - can be closed with a tight-fitting, puncture-resistant lid, without sharps being able to come out,
  - upright and stable during use,
  - leak-resistant, and
  - properly labeled to warn of hazardous waste inside the container.
- When your sharps disposal container is almost full, you will need to follow your community guidelines for the right way to dispose of your sharps disposal container. There may be state or local laws about how you should throw away used needles and syringes. For more information about safe sharps disposal, and for specific information about sharps disposal in the state that you live in, go to the FDA's website at: http://www.fda.gov/safesharpsdisposal.
- Do not dispose of your used sharps disposal container in your household trash unless your community guidelines permit this. Do not recycle your used sharps disposal container.

Manufactured by:
sanofi-aventis U.S. LLC
Morristown, NJ 07960
A SANOFI COMPANY
U.S. License No. 1752

©2025 Sanofi. All rights reserved.
All trademarks mentioned in this document are the property of the Sanofi group with the exception of BD Ultra-Fine, Clickfine, Unifine, and Pentips.

This Instructions for Use has been approved by the U.S. Food and Drug Administration.

Approved: May 2025

PRINCIPAL DISPLAY PANEL - 10 mL Vial Carton

NDC 0024-5927-00

Rx only

Merilog™

(insulin aspart-szjj) injection

100 units/mL (U-100)

For subcutaneous injection only

Use only with a U-100 syringe

One 10 mL multiple-dose vial

sanofi

PRINCIPAL DISPLAY PANEL - 3 mL Pen Carton

Rx only

NDC 0024-5928-05

Merilog™ SoloStar®
(insulin aspart-szjj) injection

For Single Patient Use Only

100 units/mL (U-100)

For subcutaneous injection only
Do not mix with other insulins
Needles not included
Dispense in this sealed carton

Five 3 mL Prefilled Pens

sanofi